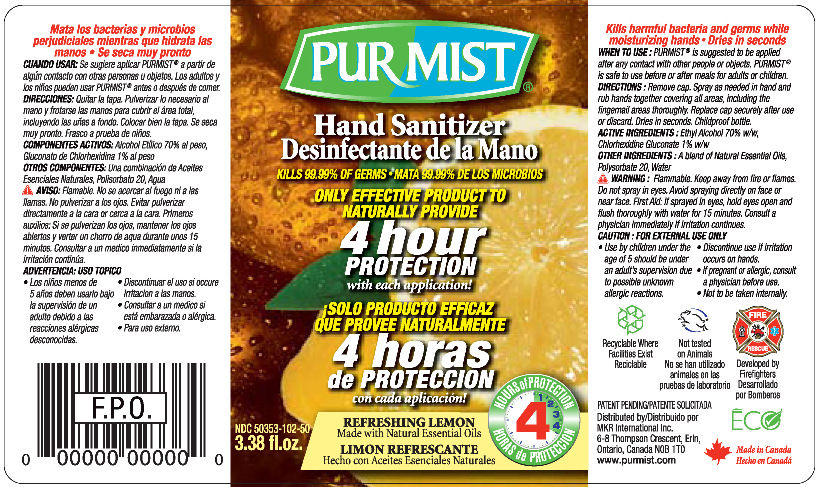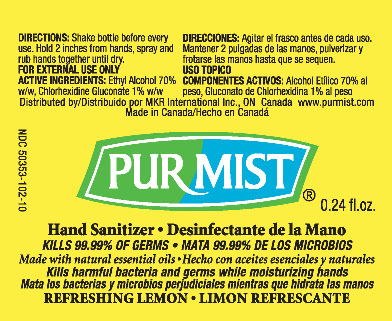 DRUG LABEL: Purmist
NDC: 50353-102 | Form: SOLUTION
Manufacturer: MKR International Inc
Category: otc | Type: HUMAN OTC DRUG LABEL
Date: 20100601

ACTIVE INGREDIENTS: ALCOHOL .7 g/1 mL; CHLORHEXIDINE GLUCONATE .01 g/1 mL
INACTIVE INGREDIENTS: POLYSORBATE 20; WATER

Hand Sanitizer

WHEN USING

WHEN TO USE: PURMIST® is suggested to be applied after any contact with other people or objects. PURMIST® is safe to use before or after meals for adults or children.

DIRECTIONS: Remove cap. Spray as needed in hand and rub hands together covering all areas, including the fingernail areas thoroughly. Replace cap securely after use or discard. Dries in seconds. Childproof bottle.

ACTIVE INGREDIENT

ACTIVE INGREDIENTS: Ethyl Alcohol 70% w/w, Chlorhexidine Gluconate 1% w/w

OTHER INGREDIENTS: A blend of Natural Essential Oils, Polysorbate 20, Water

DO NOT USE

WARNING: Flammable. Keep away from fire or flames. Do not spray in eyes. Avoid spraying directly on face or near face. First Aid: If sprayed in eyes, hold eyes open and flush thoroughly with water for 15 minutes. Consult a physician immediately if irritation continues.

CAUTION: FOR EXTERNAL USE ONLY

- Use by children under the age of 5 should be under an adult's supervision due to possible unknown allergic reactions.
- Discontinue use if irritation occurs on hands.
- If pregnant or allergic, consult a physician before use.
- Not to be taken internally.

PURMIST® 7.1mL / 0.24 fl. oz

NDC 50353-102-10

PURMIST® 0.24 fl. oz

Hand Sanitizer
KILLS 99.99% OF GERMS
Made with natural essential oils
Kills harmful bacteria and germs while moisturizing hands
REFRESHING LEMON

PURMIST® 100mL / 3.38 fl. oz

PURMIST®
Hand Sanitizer
KILLS 99.99% OF GERMS
ONLY EFFECTIVE PRODUCT TO
NATURALLY PROVIDE
4 hour
PROTECTION
with each application!
REFRESHING LEMON
Made with Natural Essential Oils

NDC 50353-102-50
3.38 fl.oz.